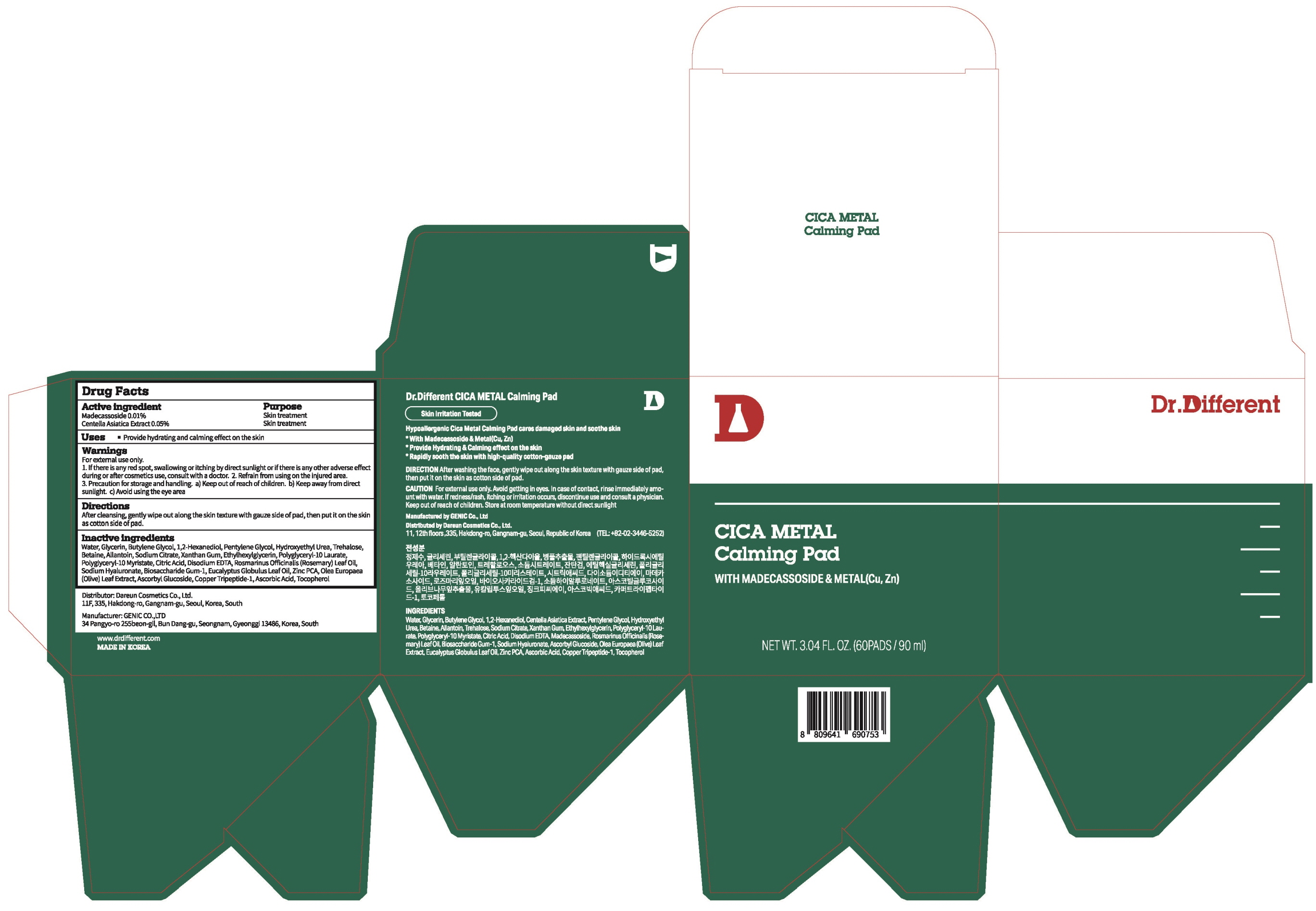 DRUG LABEL: Dr.Different CICA Metal Calming Pad
NDC: 81710-100 | Form: LIQUID
Manufacturer: Dareun Cosmetics Co., Ltd.
Category: otc | Type: HUMAN OTC DRUG LABEL
Date: 20210910

ACTIVE INGREDIENTS: Madecassoside 0.009 g/90 mL; Centella Asiatica 0.045 g/90 mL
INACTIVE INGREDIENTS: WATER; Butylene Glycol; Glycerin

ACTIVE INGREDIENTS

Madecassoside 0.01%
Centella Asiatica Extract 0.05%

INACTIVE INGREDIENTS

Water, Glycerin, Butylene Glycol, 1,2-Hexanediol, Pentylene Glycol, Hydroxyethyl Urea, Trehalose, Betaine, Allantoin, Sodium Citrate, Xanthan Gum, Ethylhexylglycerin, Polyglyceryl-10 Laurate, Polyglyceryl-10 Myristate, Citric Acid, Disodium EDTA, Rosmarinus Officinalis (Rosemary) Leaf Oil, Sodium Hyaluronate, Biosaccharide Gum-1, Eucalyptus Globulus Leaf Oil, Zinc PCA, Olea Europaea (Olive) Leaf Extract, Ascorbyl Glucoside, Copper Tripeptide-1, Ascorbic Acid, Tocopherol

PURPOSE

Skin treatment

WARNINGS

For external use only.
1. If there is any red spot, swallowing or itching by direct sunlight or if there is any other adverse effect during or after cosmetics use, consult with a doctor.
2. Refrain from using on the injured area.
3. Precaution for storage and handling.
a) Keep out of reach of children.
b) Keep away from direct sunlight.
c) Avoid using the eye area

KEEP OUT OF REACH OF CHILDREN

Uses

■ Provide hydrating and calming effect on the skin

Directions

After cleansing, gently wipe out along the skin texture with gauze side of pad, then put it on the skin as cotton side of pad.